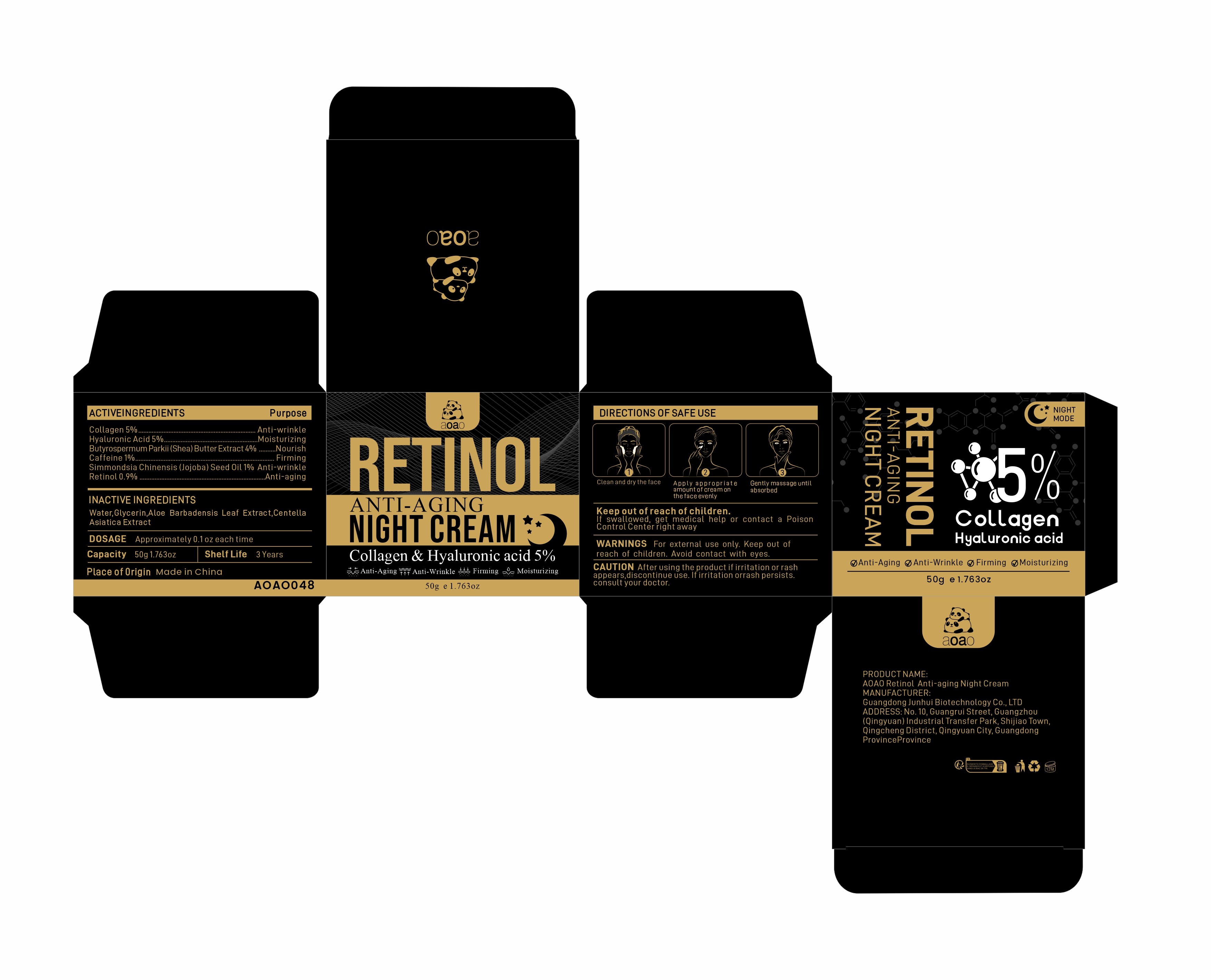 DRUG LABEL: AOAO Retinol Anti-aging Night Cream
NDC: 84509-027 | Form: CREAM
Manufacturer: Guangdong Junhui Biotechnology Co., LTD
Category: otc | Type: HUMAN OTC DRUG LABEL
Date: 20241021

ACTIVE INGREDIENTS: HYALURONIC ACID 2500 mg/50 g; CAFFEINE 500 mg/50 g; COLLAGEN, SOLUBLE, FISH SKIN 2500 mg/50 g; SHEA BUTTER 2000 mg/50 g; JOJOBA OIL 500 mg/50 g; RETINOL 450 mg/50 g
INACTIVE INGREDIENTS: GLYCERIN; ALOE VERA LEAF; CENTELLA ASIATICA TRITERPENOIDS; WATER

Active Ingredients

Collagen 5%
Butyrospermum Parkii (Shea) Butter Extract 4%
Hyaluronic Acid 5%
Caffeine 1%
Simmondsia Chinensis (Jojoba) Seed Oil 1%
Retinol 0.9%

Purpose

Anti-wrinkle
Nourish
Moisturizing
Firming
Anti-aging

Uses

1、Clean and dry the face
2、Apply an appropriateamount of face cream evenly on the face
3、Gently massage until absorbed

Warnings

For external use only. Keep out ofreach of children.Avoid contact with eyes.

Keep out of reach of children

If swallowed, get medical help or contact a Poison Control Center right away

CAUTION

After using the product if irritation or rash appears,discontinue use.If irritation or
rash persists.consult your doctor.

DOSAGE

Approximately 0.1 oz each time

Product Name

AOAO Retinol Anti-aging Night Cream

Inactive Ingredients

Water,Glycerin，Aloe Barbadensis Leaf Extract，Centella Asiatica Extract.

MANUFACTURER

Guangdong Junhui Biotechnology Co., LTD

ADDRESS

No. 10, Guangrui Street, Guangzhou (Qingyuan) Industrial Transfer Park, Shijiao Town, Qingcheng District, Qingyuan City, Guangdong Province

Capacity

50g e 1.763 oz

Shelf Life

3 Years

Place of Origin

Made in China